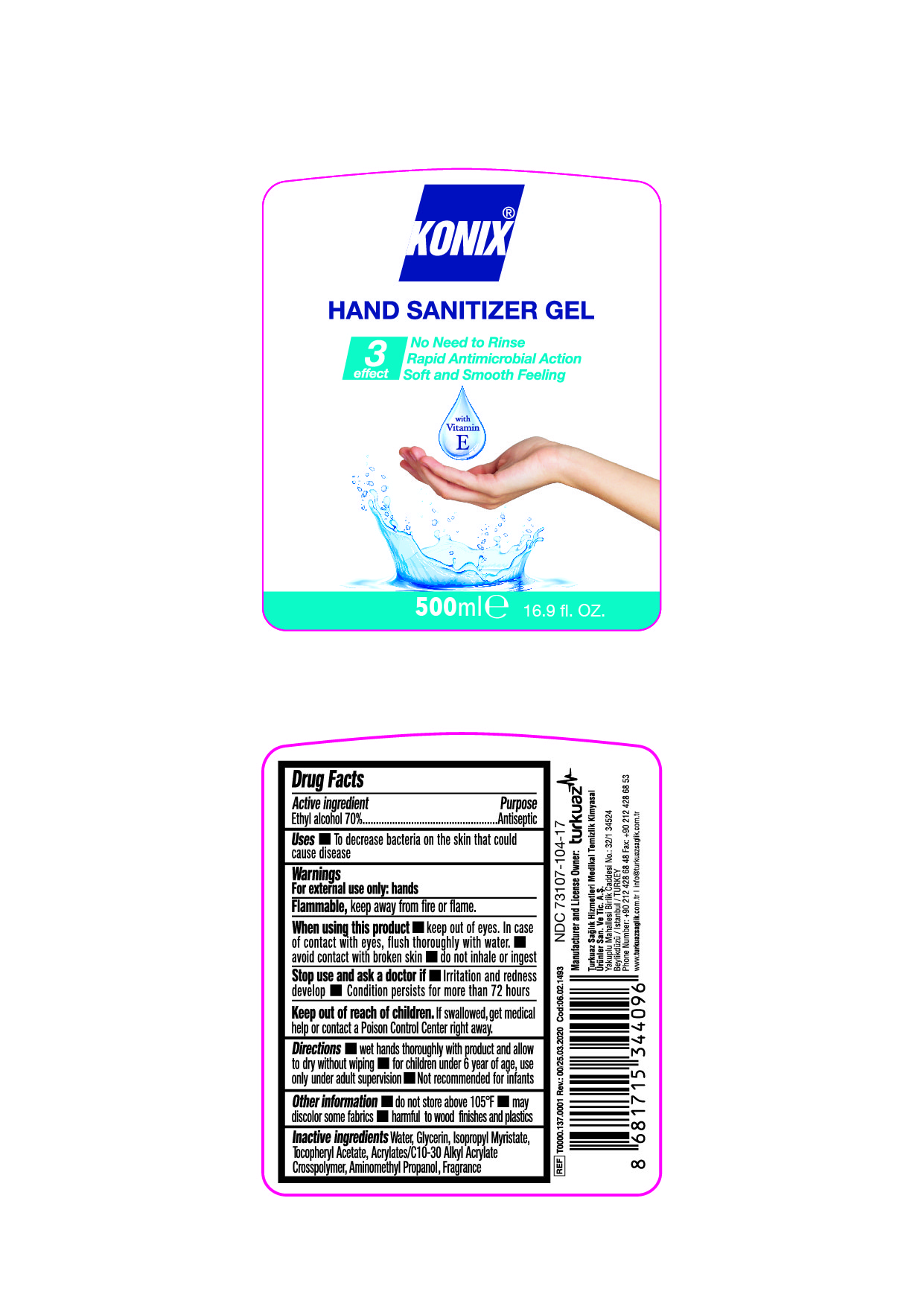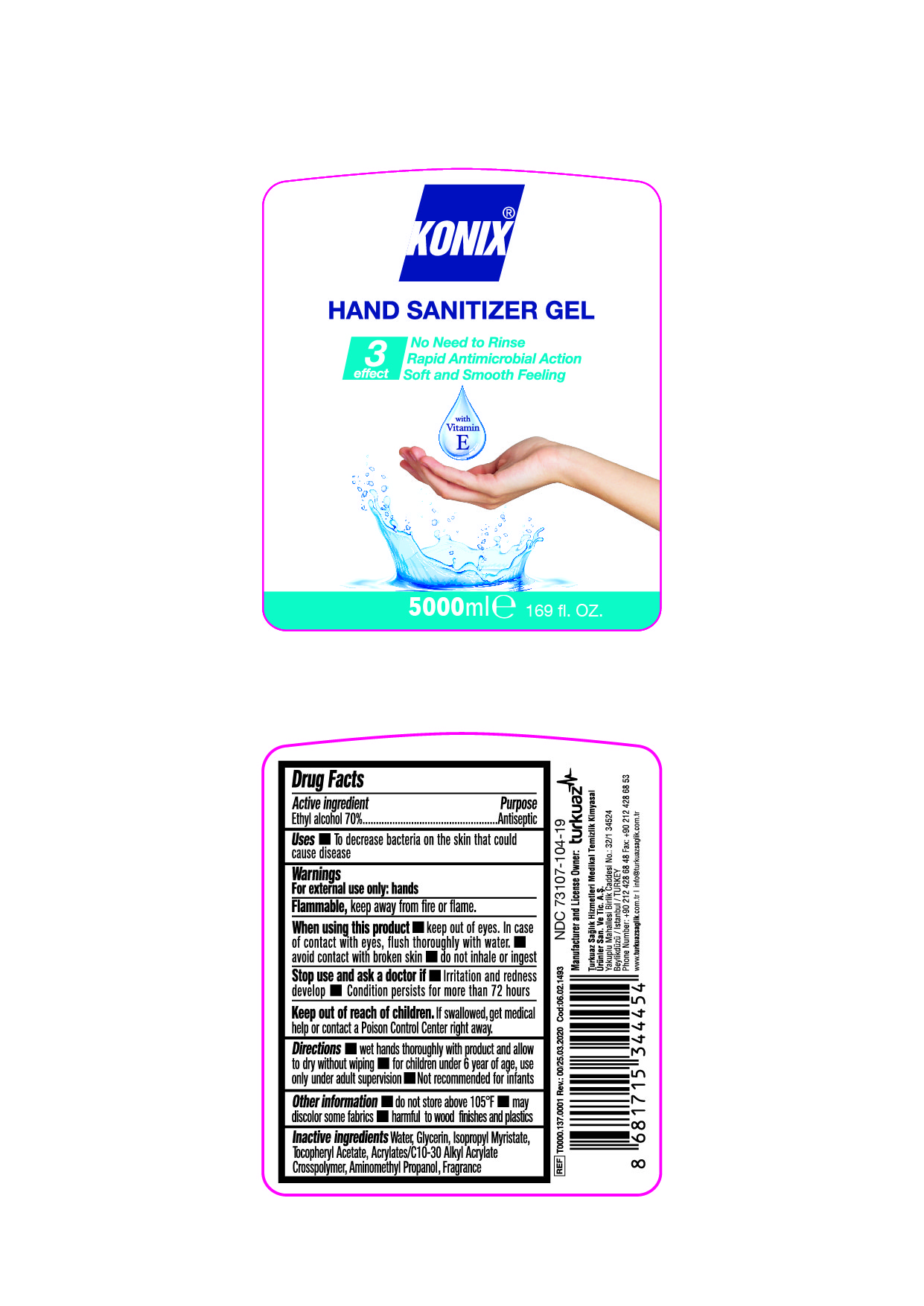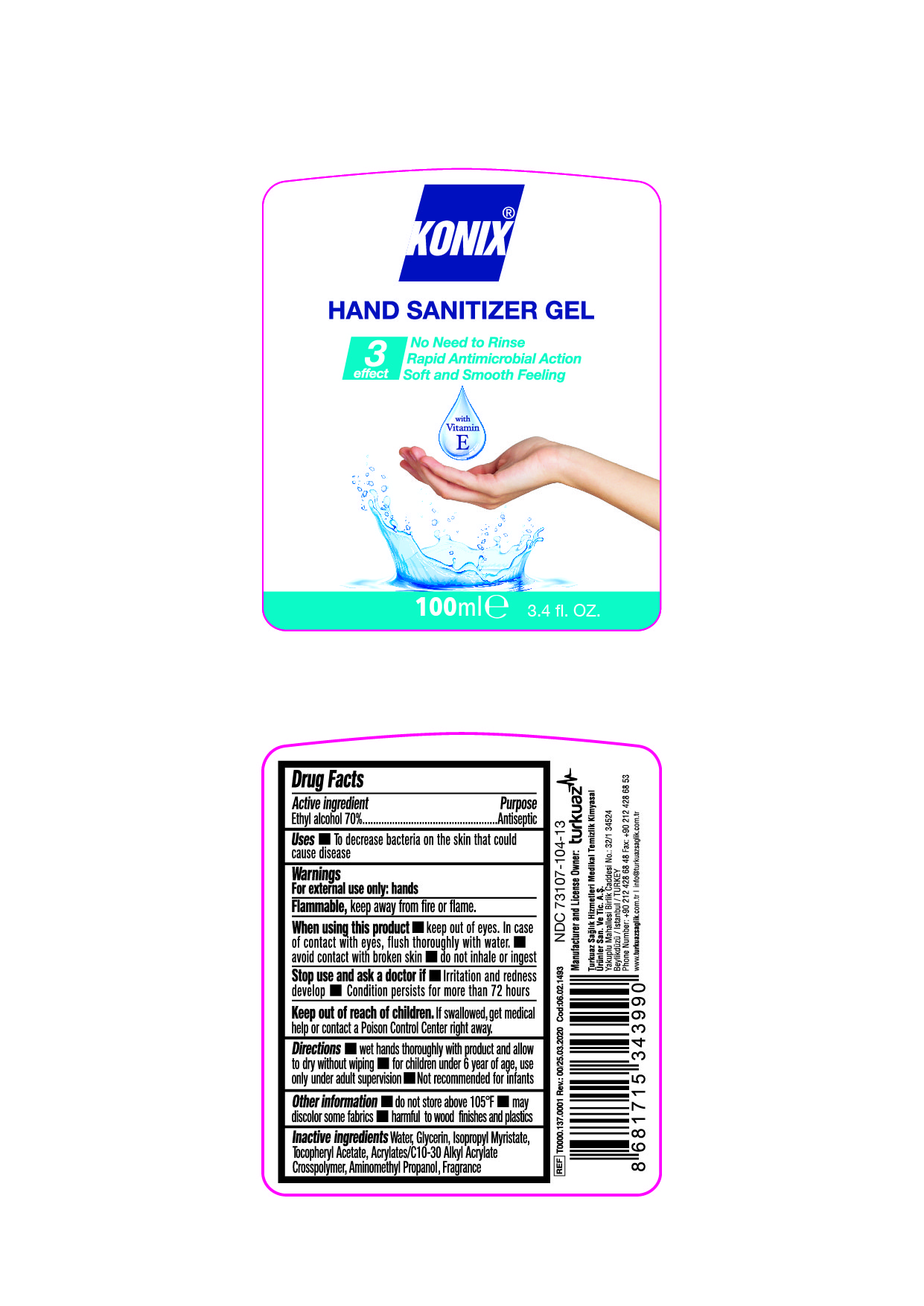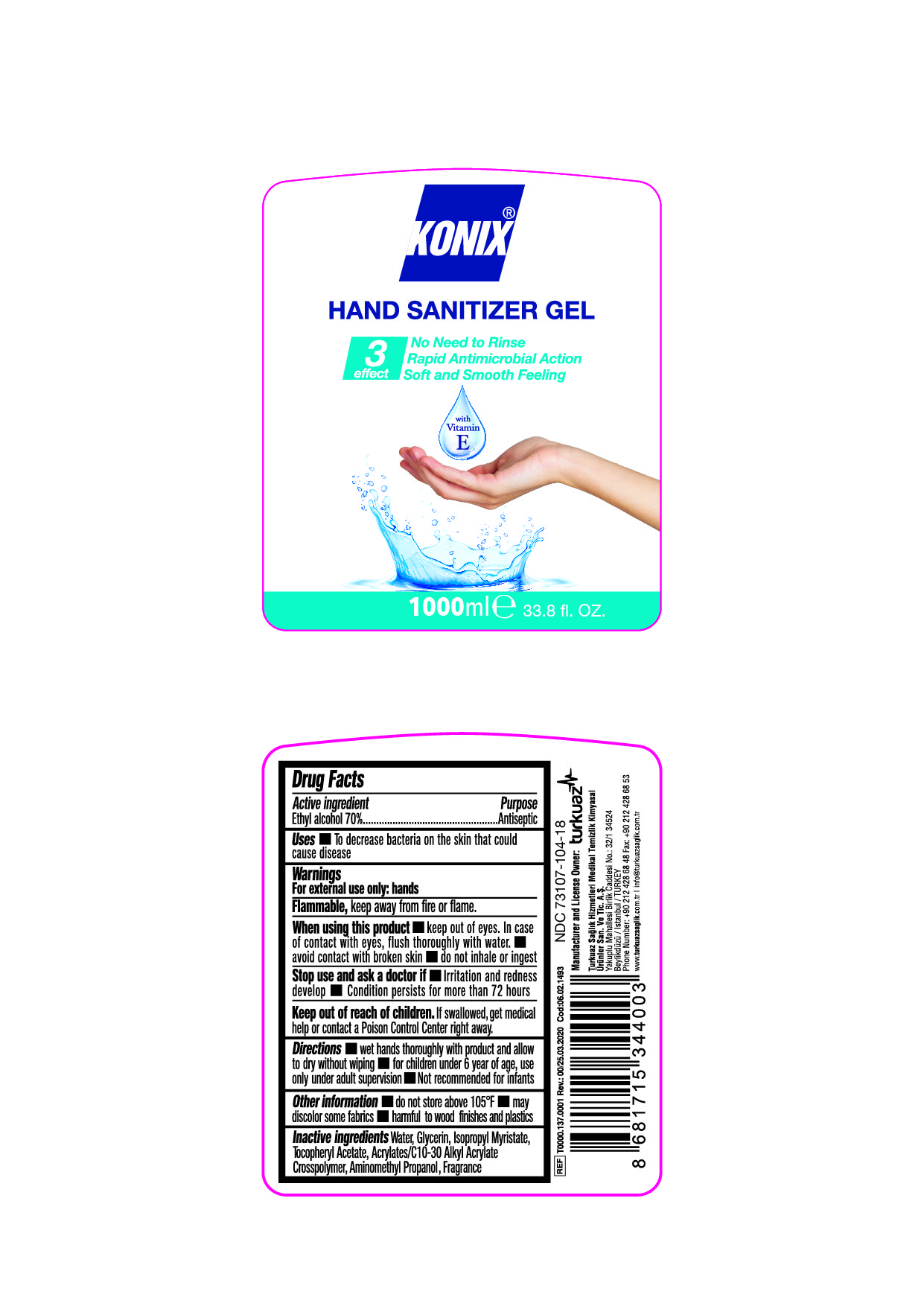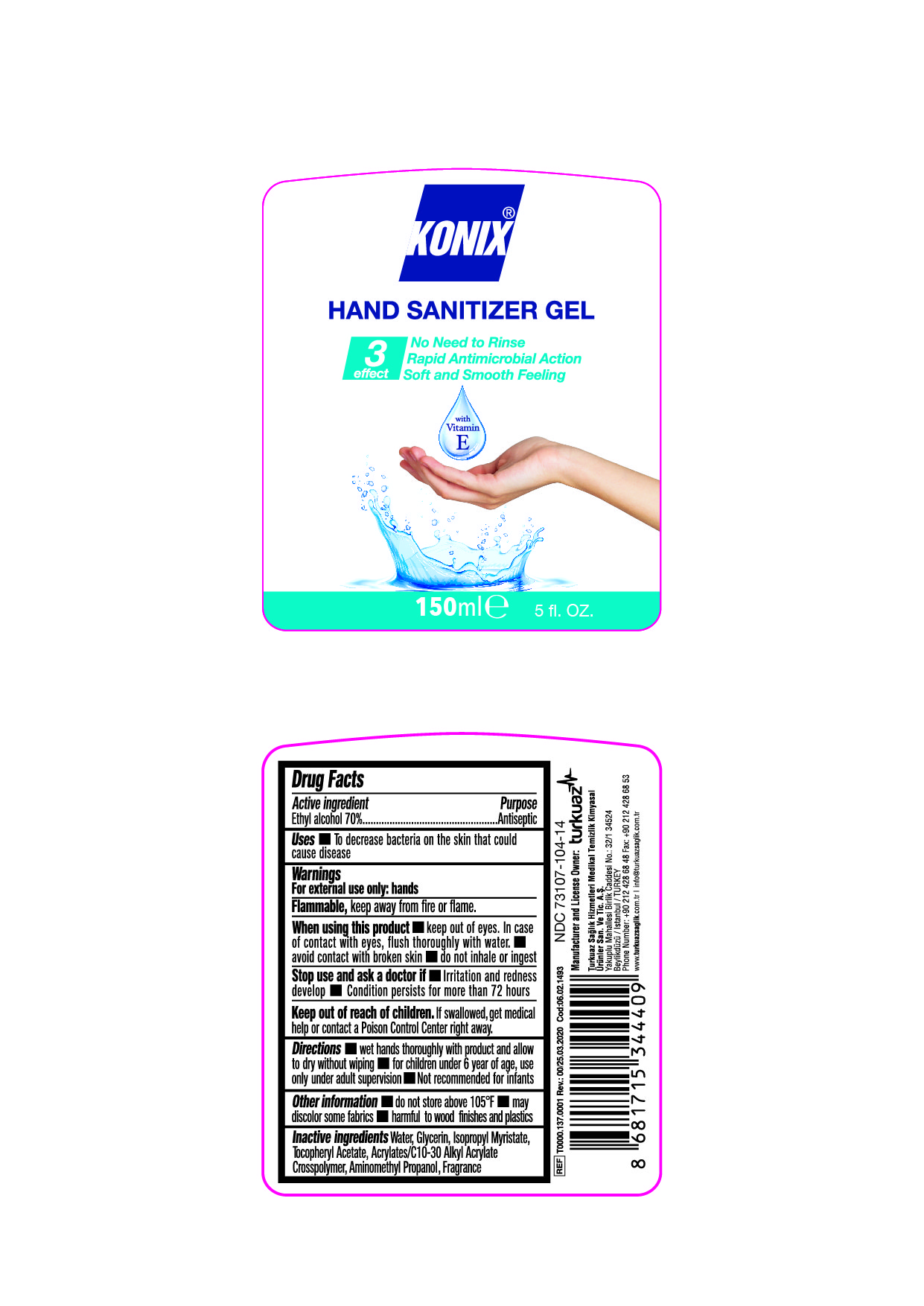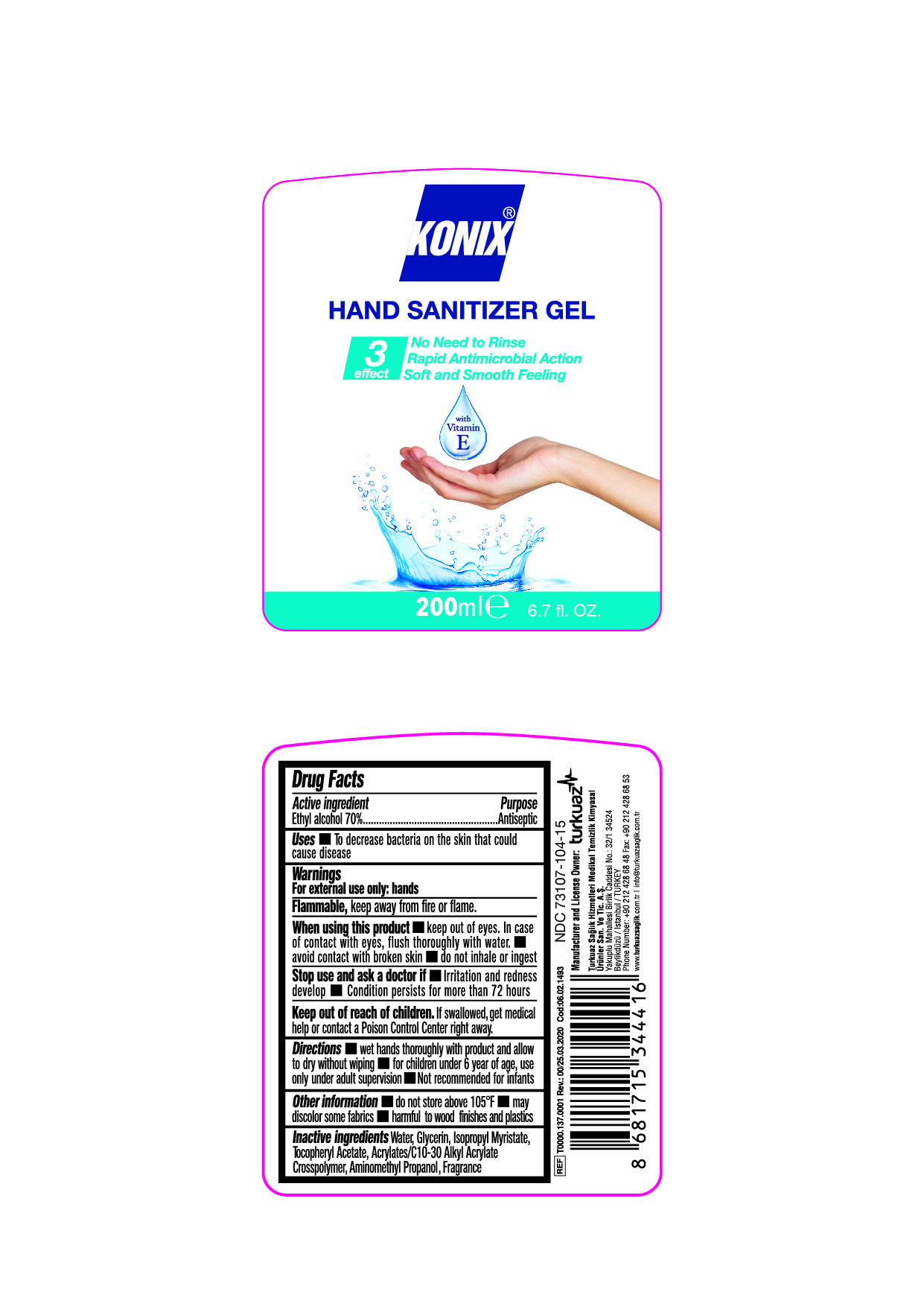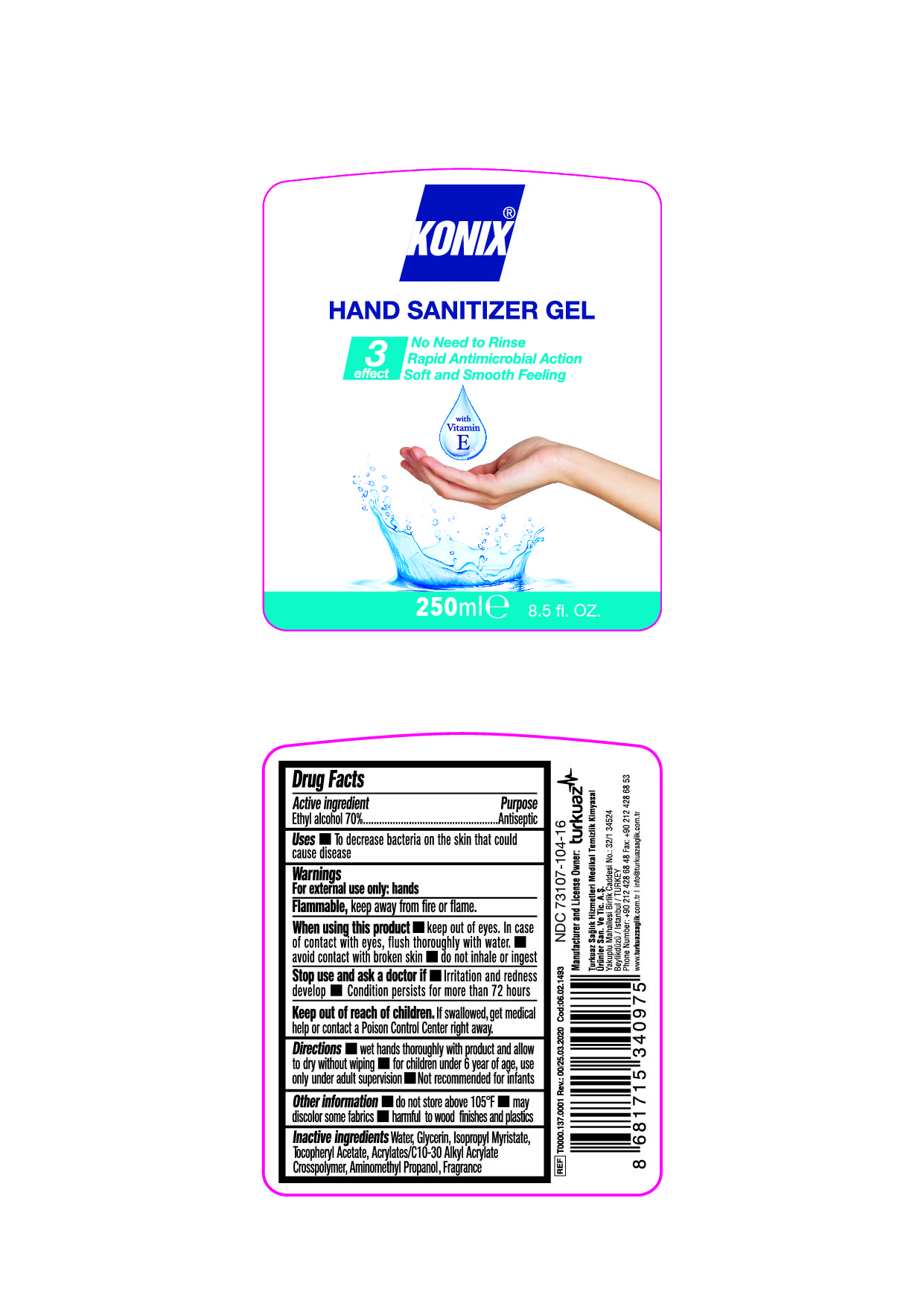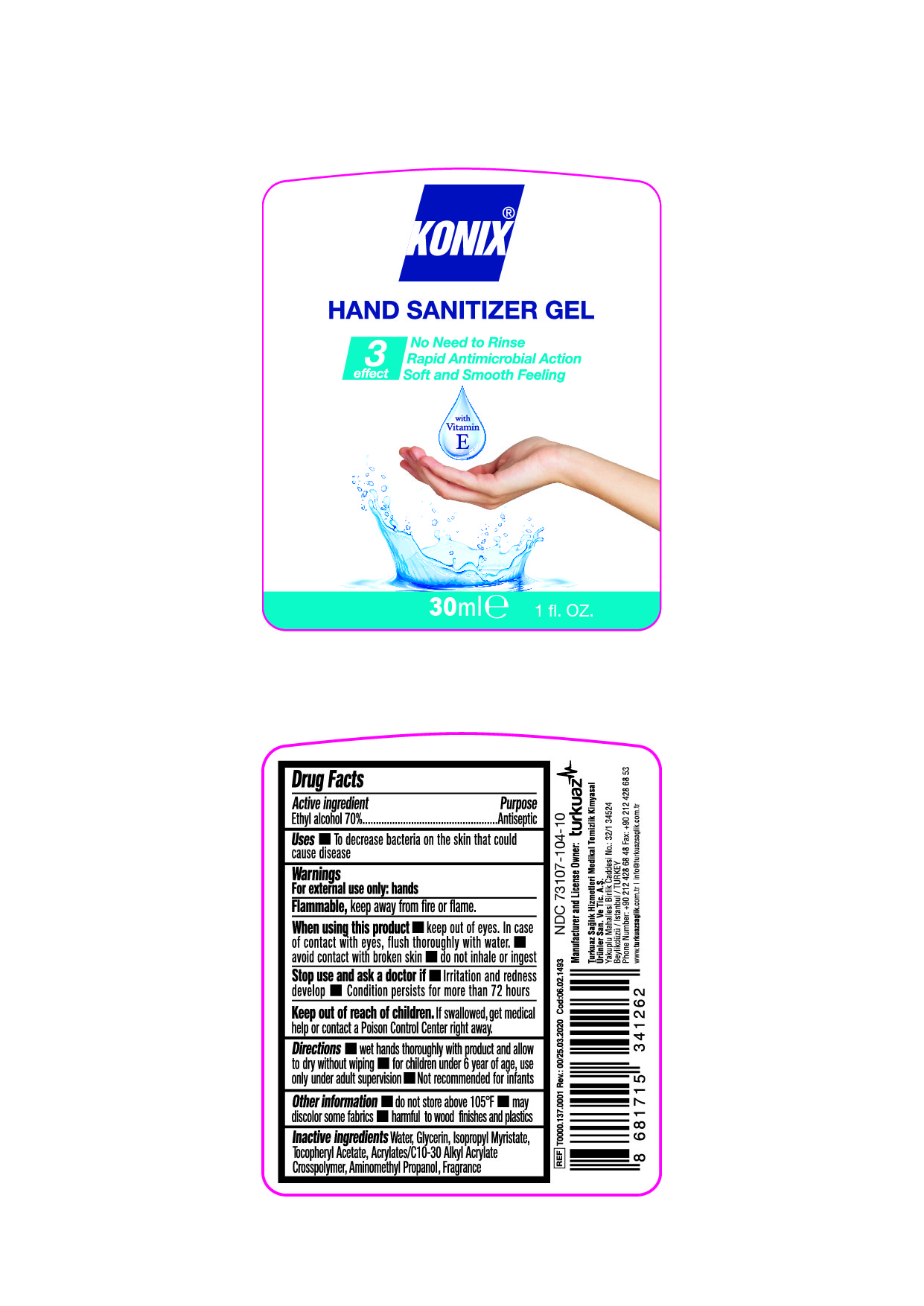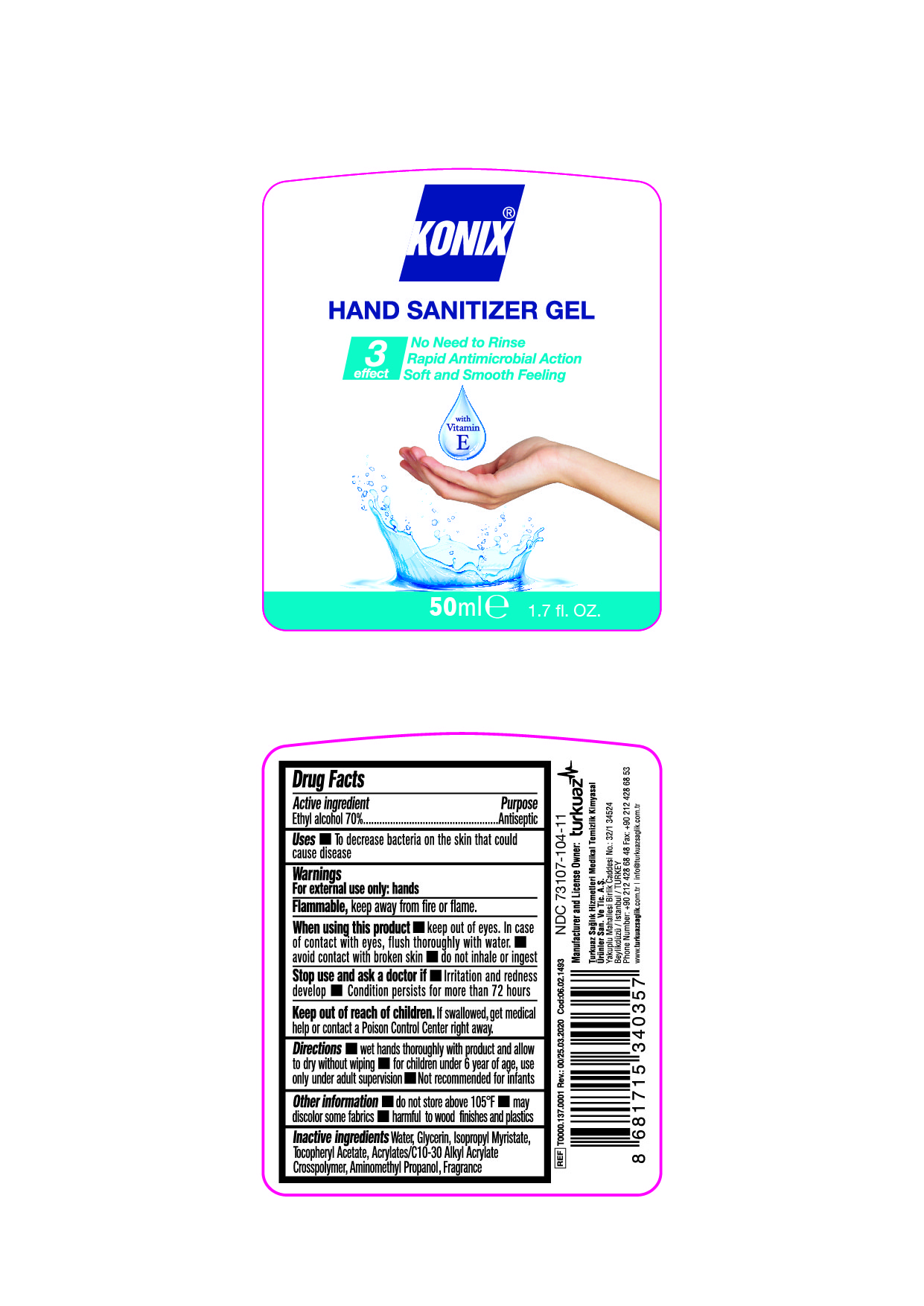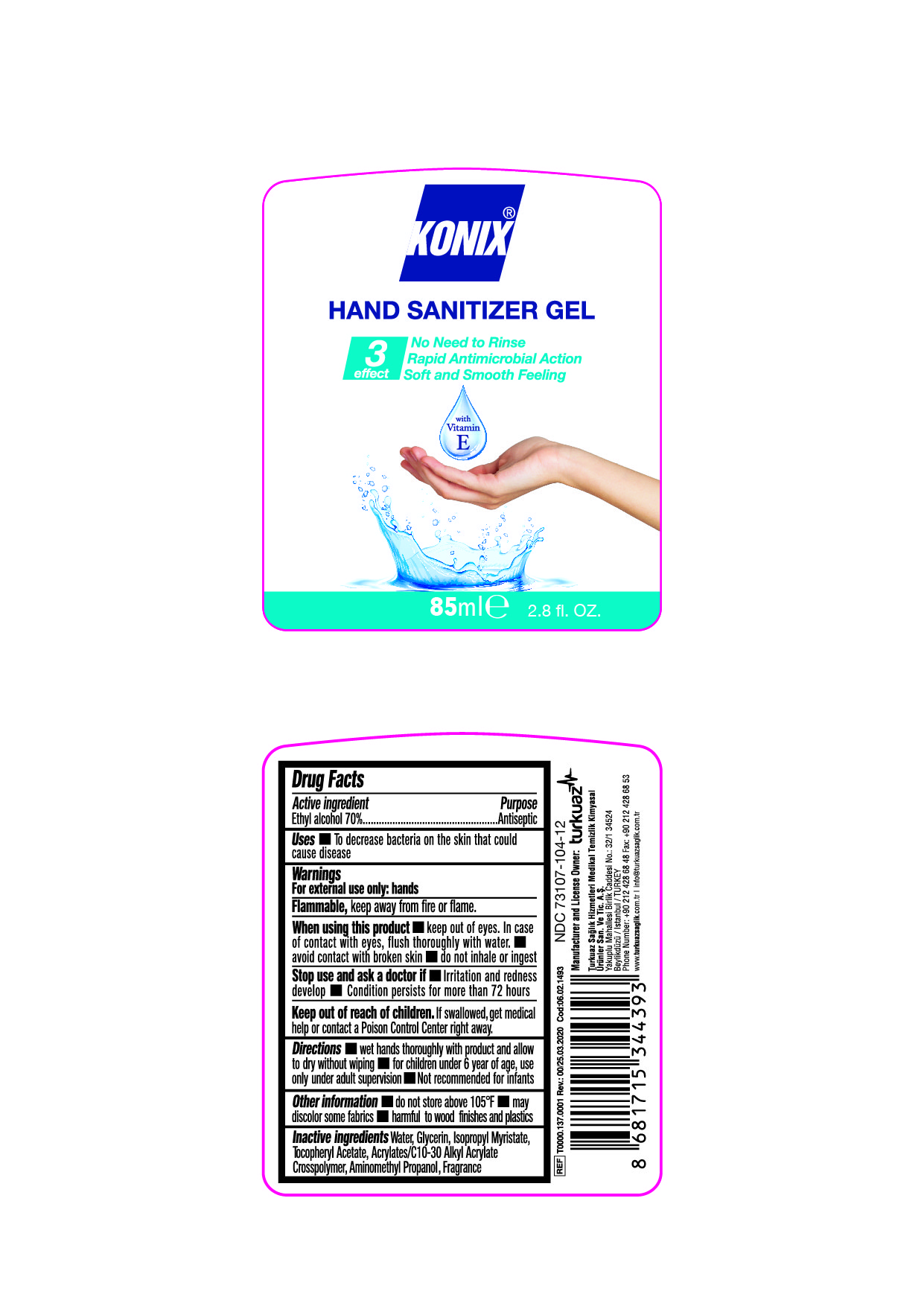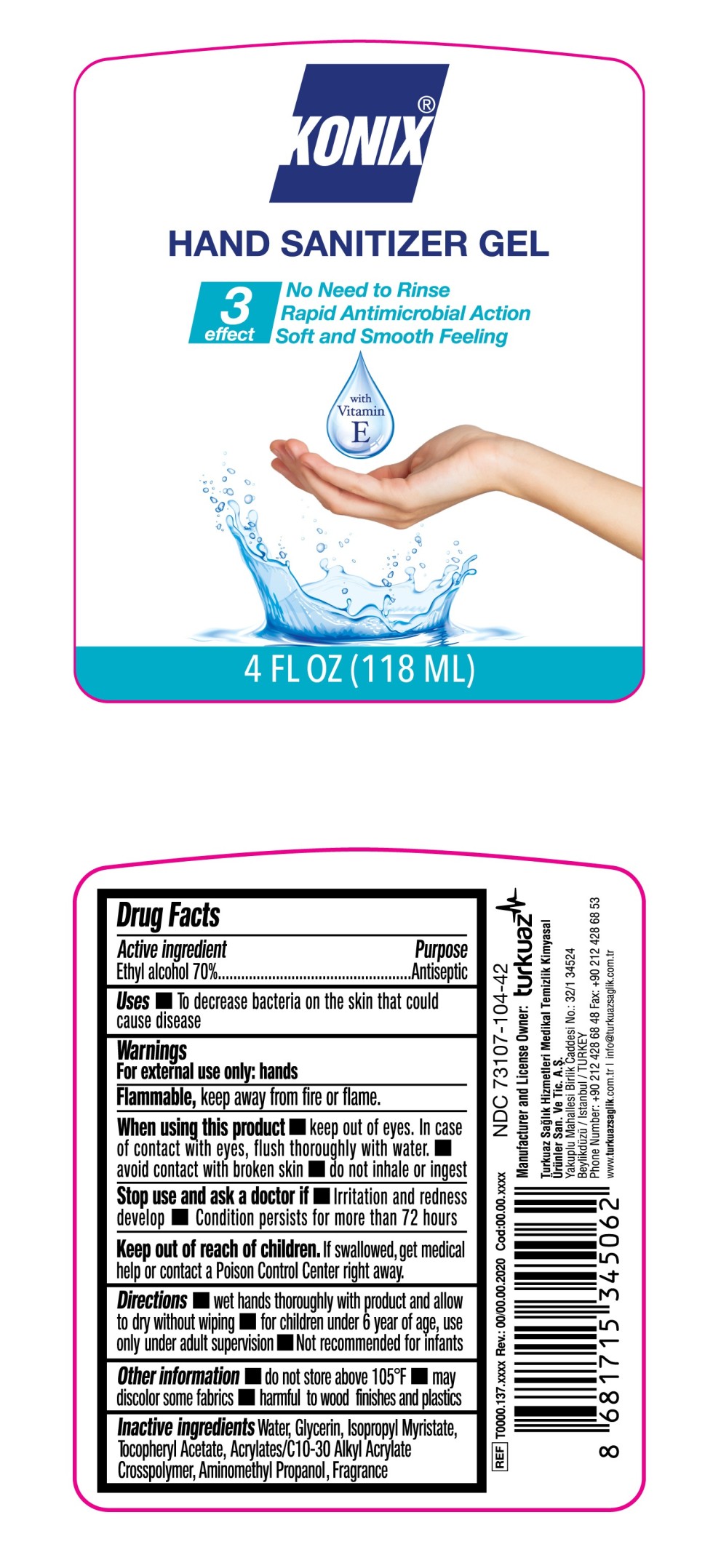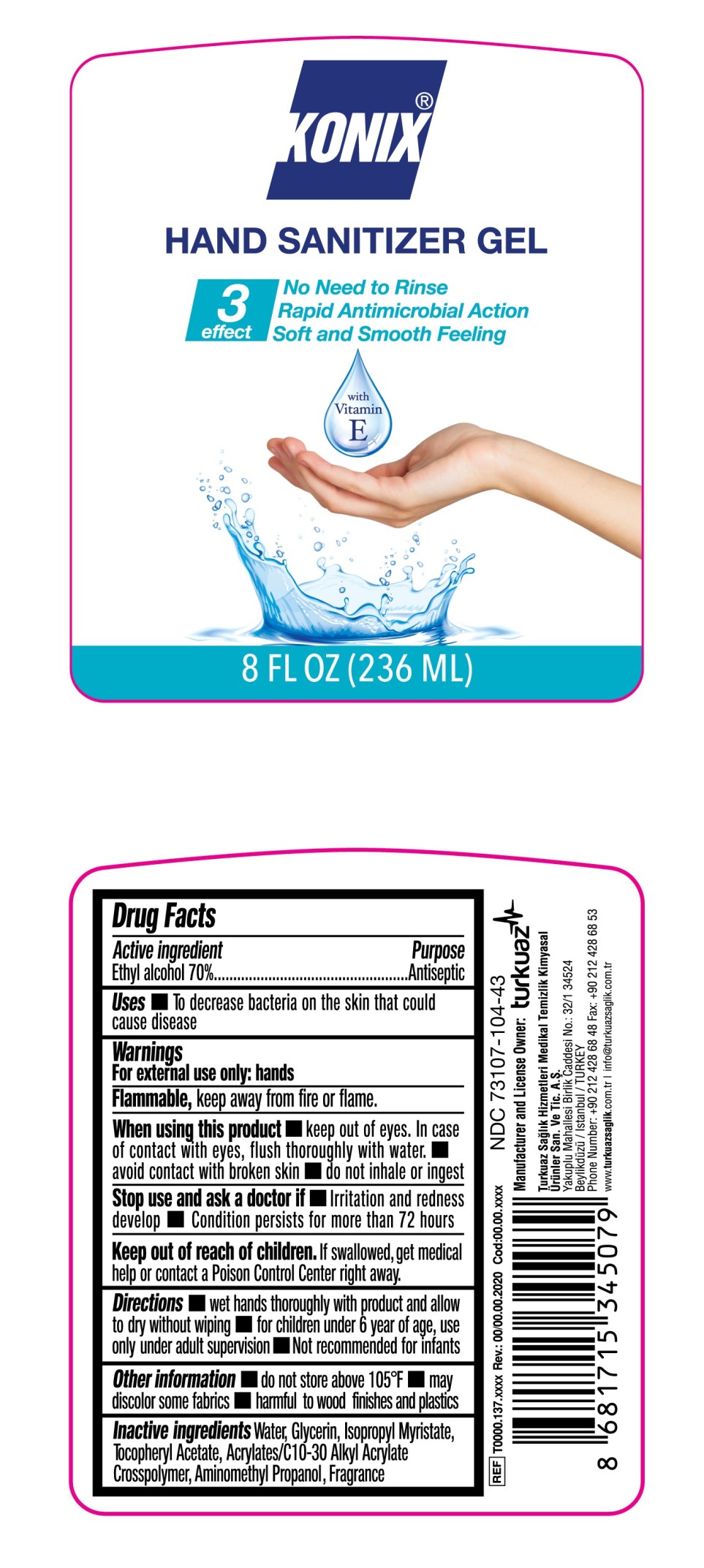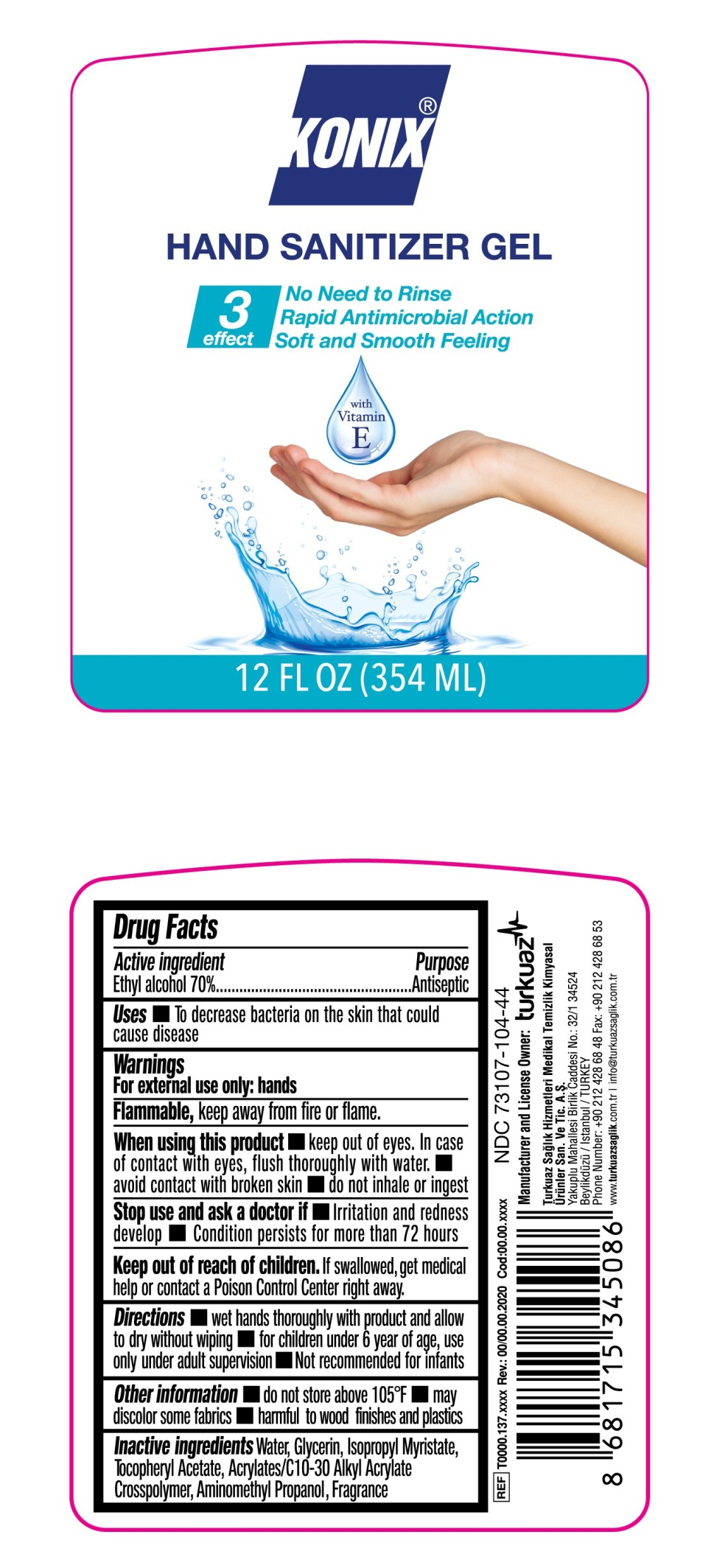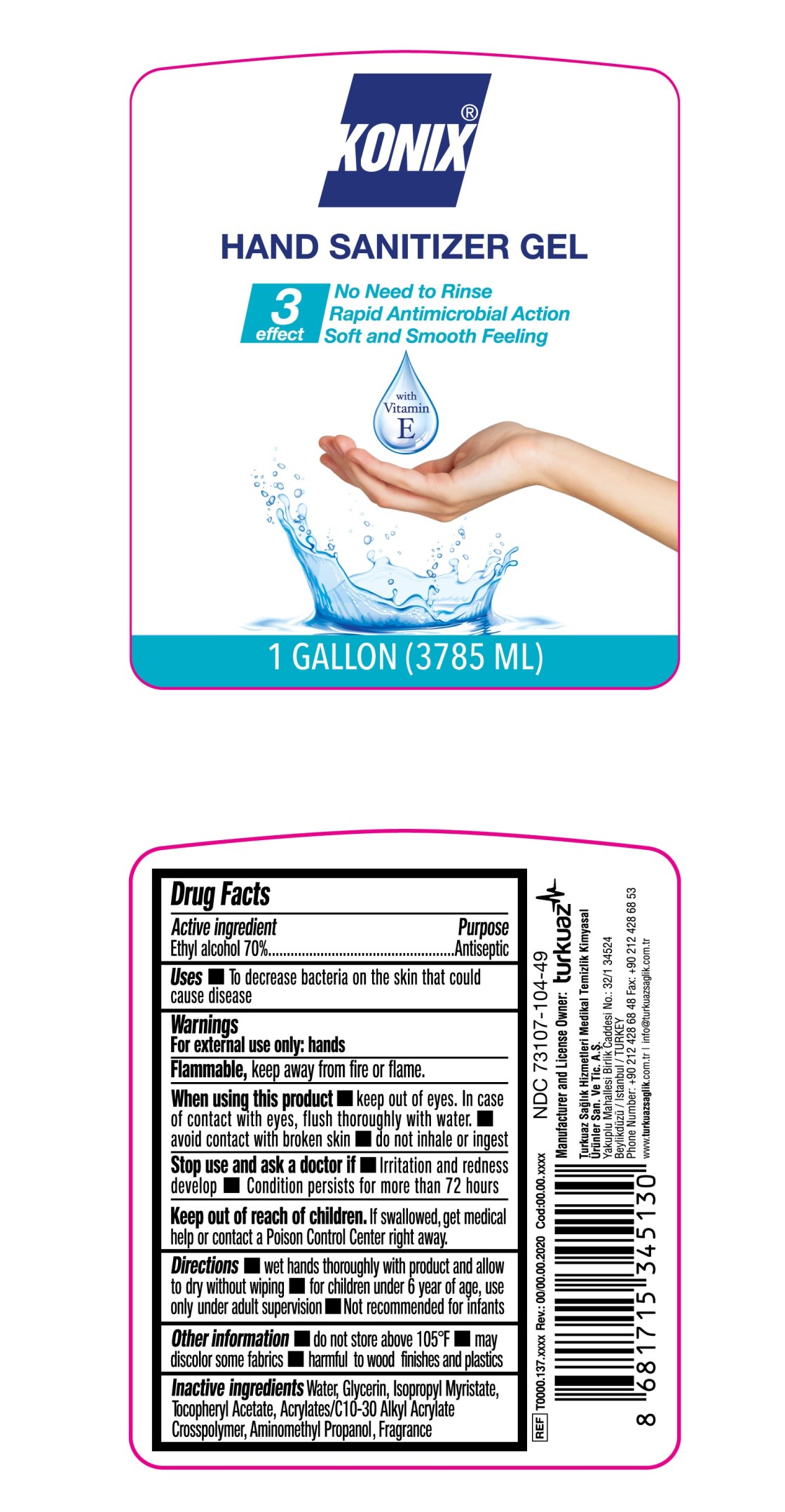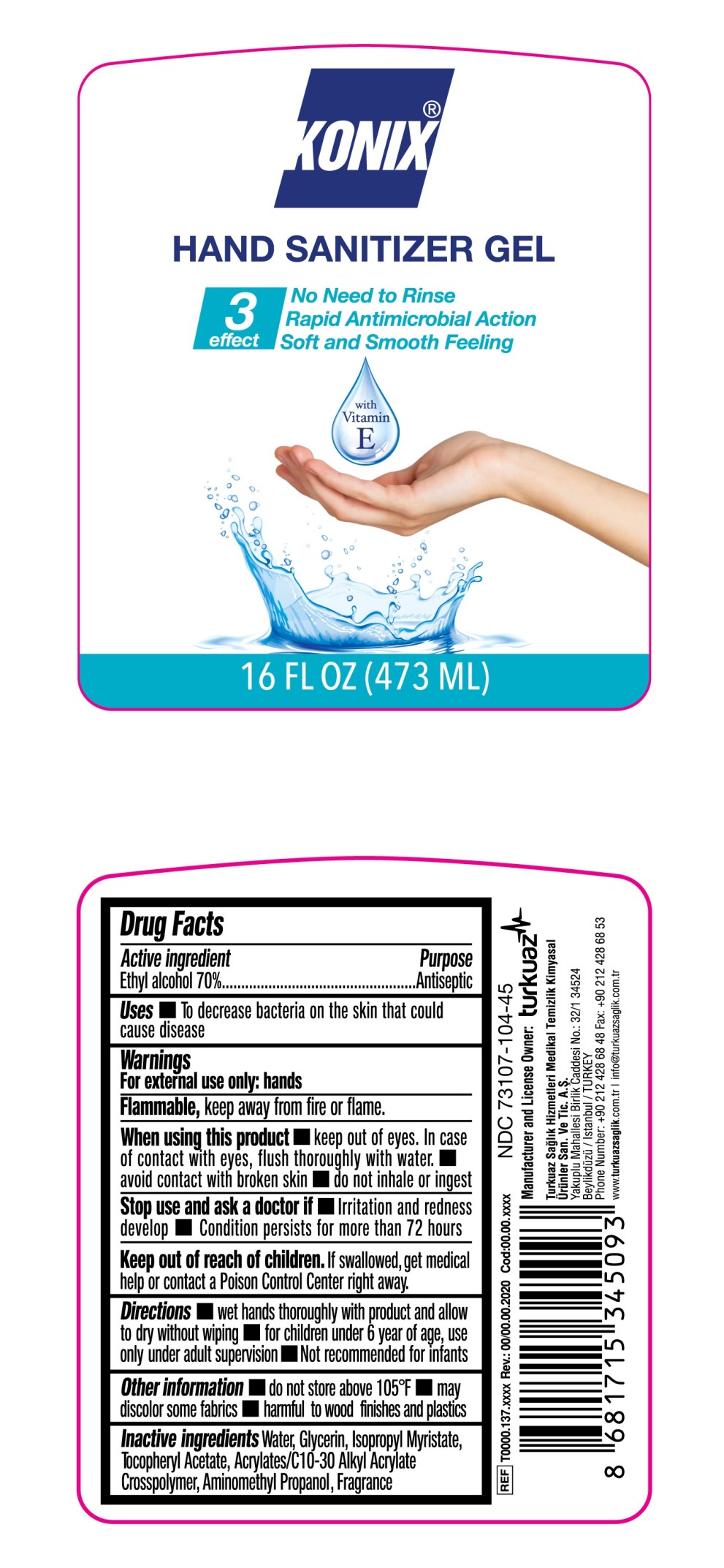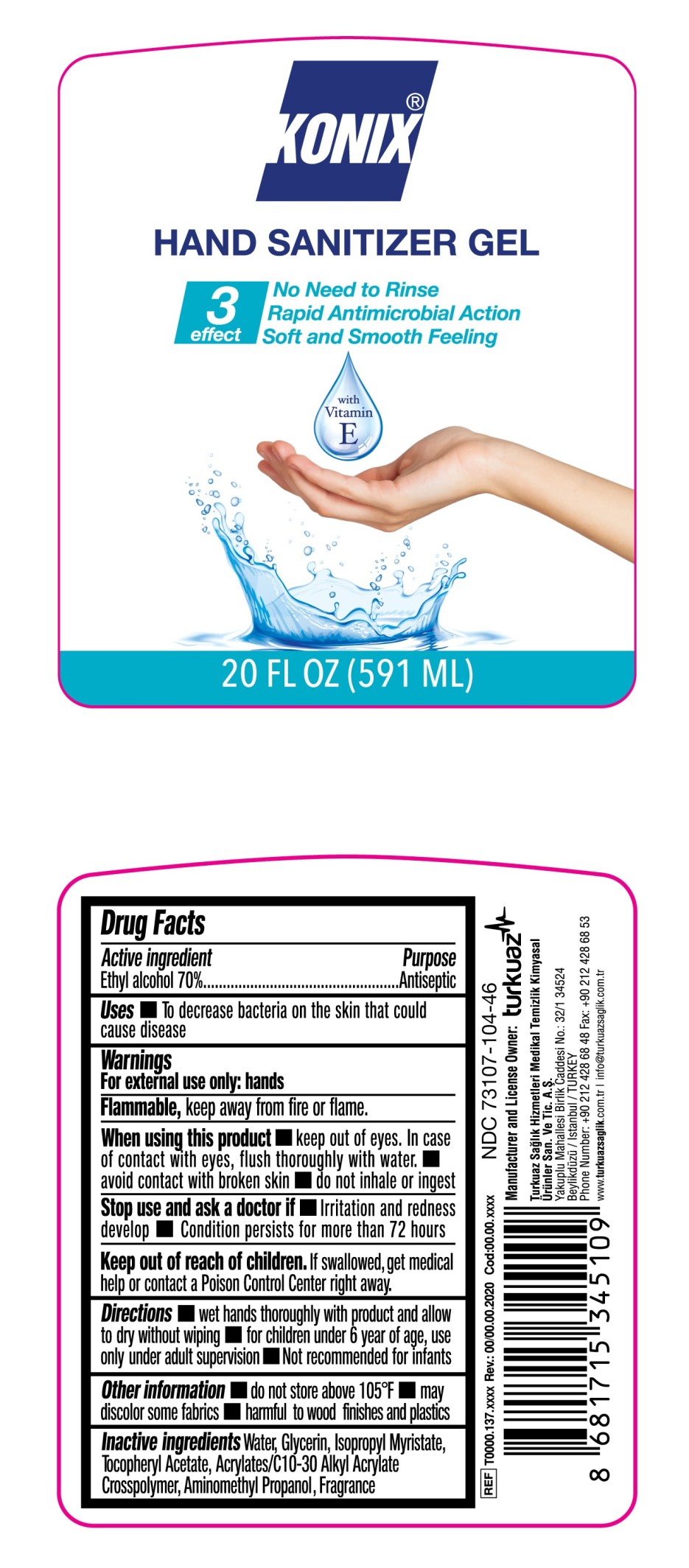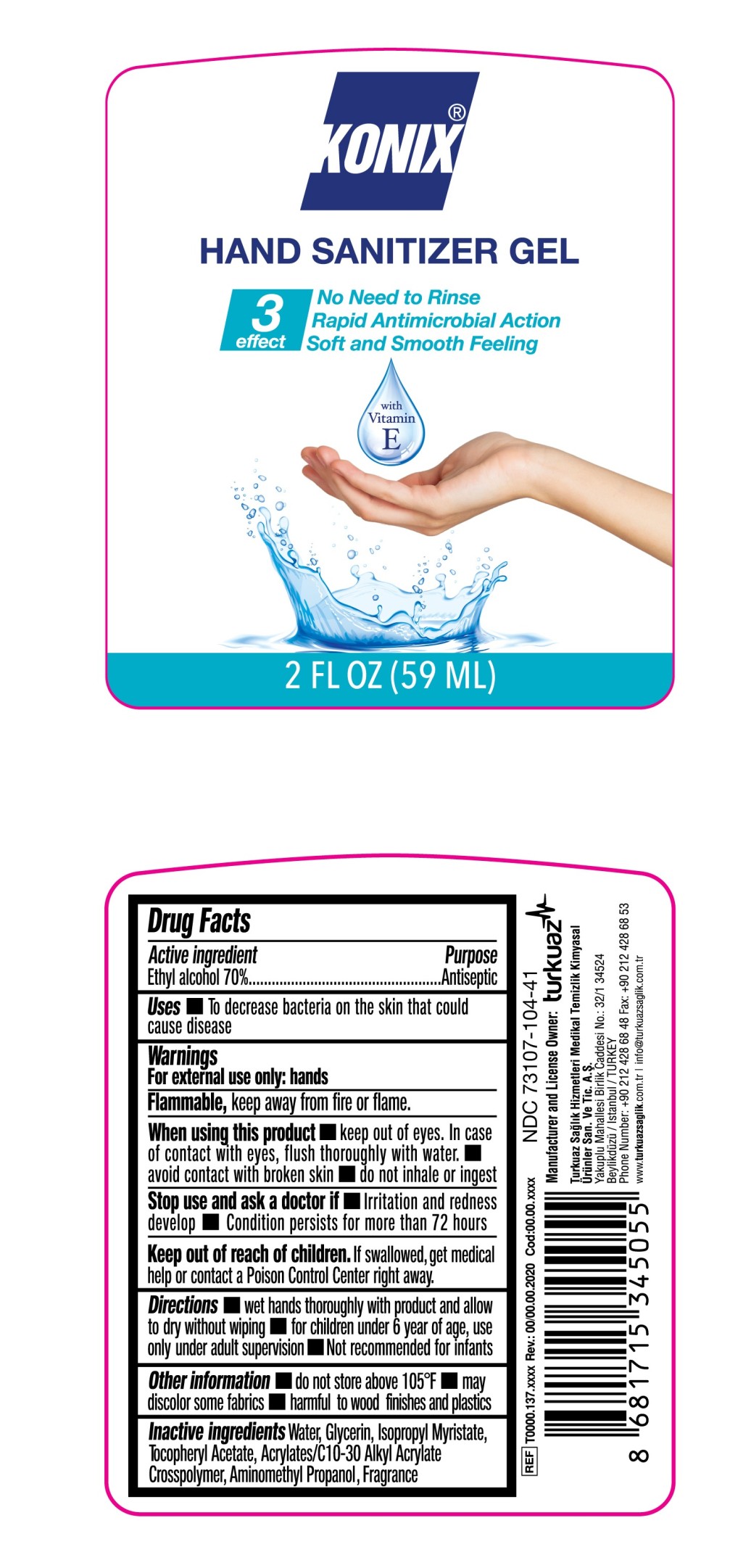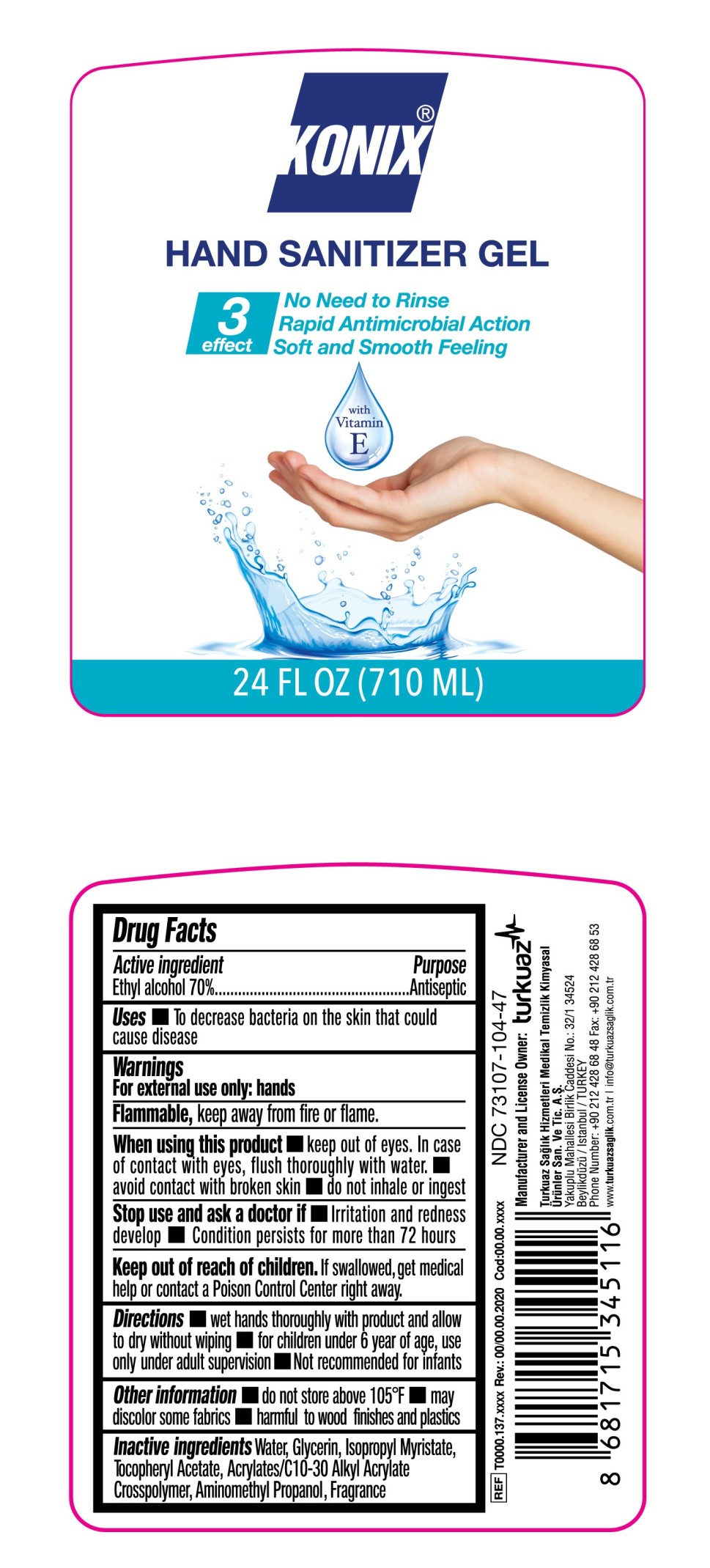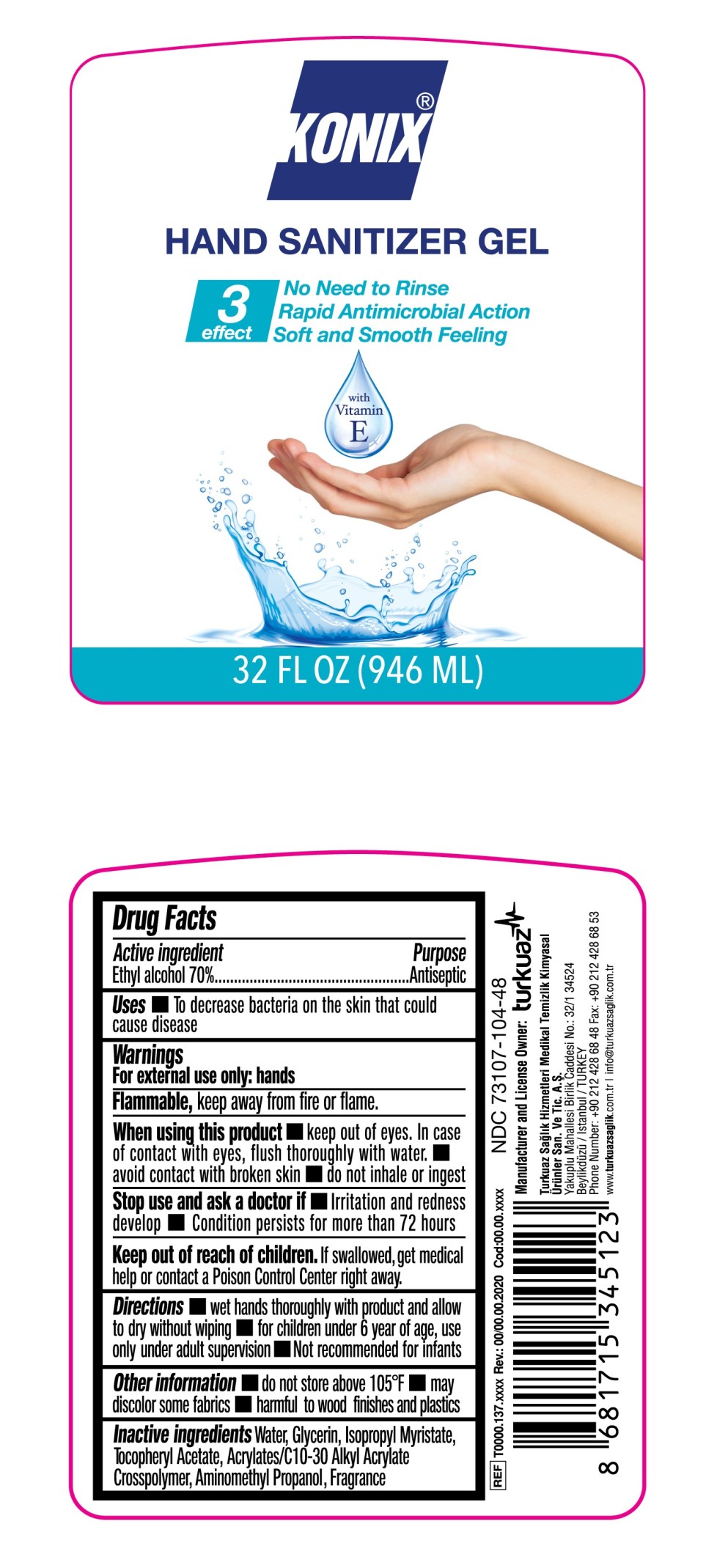 DRUG LABEL: Konix Hand Sanitizer Gel
NDC: 73107-104 | Form: GEL
Manufacturer: Turkuaz Saglik Hizmetleri Medikal Temizlik Kimyasal Urunler Sanayi ve Tic. AS
Category: otc | Type: HUMAN OTC DRUG LABEL
Date: 20200519

ACTIVE INGREDIENTS: ALCOHOL 70 mL/100 mL
INACTIVE INGREDIENTS: WATER; GLYCERIN; ISOPROPYL MYRISTATE; .ALPHA.-TOCOPHEROL ACETATE; AMINOMETHYLPROPANOL; CARBOMER INTERPOLYMER TYPE A (ALLYL SUCROSE CROSSLINKED)

KONIX Hand Sanitizer Gel

Active Ingredient(s)

Ethyl alcohol 70%

Purpose

Antiseptic, Hand Sanitizer Gel

Use

Uses To decrease bacteria on the skin that could cause disease

Warnings

For external use only: hands.

Flammable, keep away from fire or flame.

When using this product keep out of eyes. In case of contact with eyes, flush thoroughly with water. avoid contact with broken skin do not inhale or ingest

Stop use and ask a doctor if Irritation and redness develop Condition persists for more than 72 hours.

Keep out of reach of children.

If swallowed, get medical help or contact a Poison Control Center right away.

Directions

wet hands thoroughly with product and allow to dry without wiping for children under 6 year of age, use only under adult supervision Not recommended for infants

Other information

- do not store above 105°F
- may discolor some fabrics
- harmful to wood finishes and plastics

Inactive ingredients

Water, Glycerin, Isopropyl Myristate,Tocopheryl Acetate, Acrylates/C10-30 Alkyl Acrylate Crosspolymer, Aminomethyl Propanol, Fragrance

PACKAGE LABEL

2 FL OZ (59 ML) NDC 73107-104-41

PACKAGE LABEL

4 FL OZ (118 ML) NDC 73107-104-42

PACKAGE LABEL

8 FL OZ (236 ML) NDC 73107-104-43

PACKAGE LABEL

12 FL OZ (354 ML) NDC 73107-104-44

PACKAGE LABEL

16 FL OZ (473 ML) NDC 73107-104-45

PACKAGE LABEL

20 FL OZ (591 ML) NDC 73107-104-46

PACKAGE LABEL

24 FL OZ (710 ML) NDC 73107-104-47

PACKAGE LABEL

32 FL OZ (946 ML) NDC 73107-104-48

PACKAGE LABEL

1 GALLON (3785 ML) NDC 73107-104-49